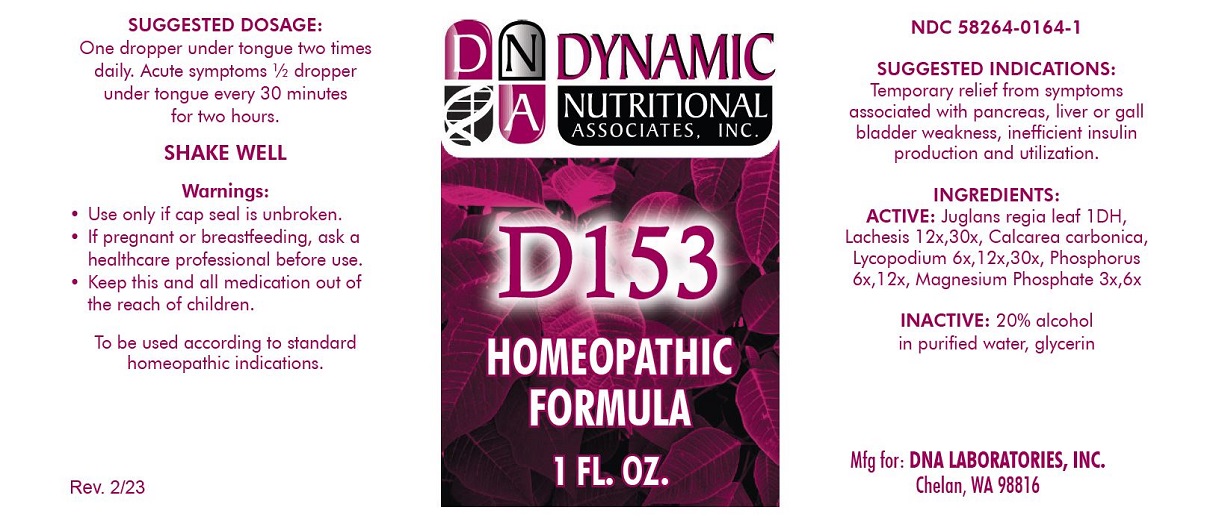 DRUG LABEL: D-153
NDC: 58264-0164 | Form: SOLUTION
Manufacturer: DNA Labs
Category: homeopathic | Type: HUMAN OTC DRUG LABEL
Date: 20250113

ACTIVE INGREDIENTS: OYSTER SHELL CALCIUM CARBONATE, CRUDE 30 [hp_X]/1 mL; JUGLANS REGIA LEAF 1 [hp_X]/1 mL; LACHESIS MUTA VENOM 30 [hp_X]/1 mL; LYCOPODIUM CLAVATUM SPORE 30 [hp_X]/1 mL; PHOSPHORUS 12 [hp_X]/1 mL; MAGNESIUM PHOSPHATE, DIBASIC TRIHYDRATE 6 [hp_X]/1 mL
INACTIVE INGREDIENTS: WATER; ALCOHOL; GLYCERIN

D-153

INDICATIONS AND USAGE

PURPOSE

Temporary relief from symptoms associated with pancreas, liver or gall bladder weakness, inefficient insulin production and utilization.

INGREDIENTS

ACTIVE

Juglans regia leaf 1DH, Lachesis 12x,30x, Calcarea carbonica, Lycopodium 6x,12x,30x, Phosphorus 6x,12x, Magnesium Phosphate 3x,6x

INACTIVE

20% alcohol in purified water, glycerin.

SUGGESTED DOSAGE

One dropper under tongue two times daily. Acute symptoms 1/2 dropper under tongue every 30 minutes for two hours.

STORAGE AND HANDLING

SHAKE WELL

Warnings

- Use only if cap seal is unbroken.

PREGNANCY OR BREAST FEEDING

- If pregant or breastfeeding, ask a healthcare professional before use.

KEEP OUT OF REACH OF CHILDREN

- Keep this and all medication out of the reach of children.

To be used according to standard homeopathic indications.

PRINCIPAL DISPLAY PANEL - 1 FL. OZ. Bottle Label

DYNAMIC

NUTRITIONAL

ASSOCIATES, INC.

D-153

HOMEOPATHIC

1 FL. OZ.